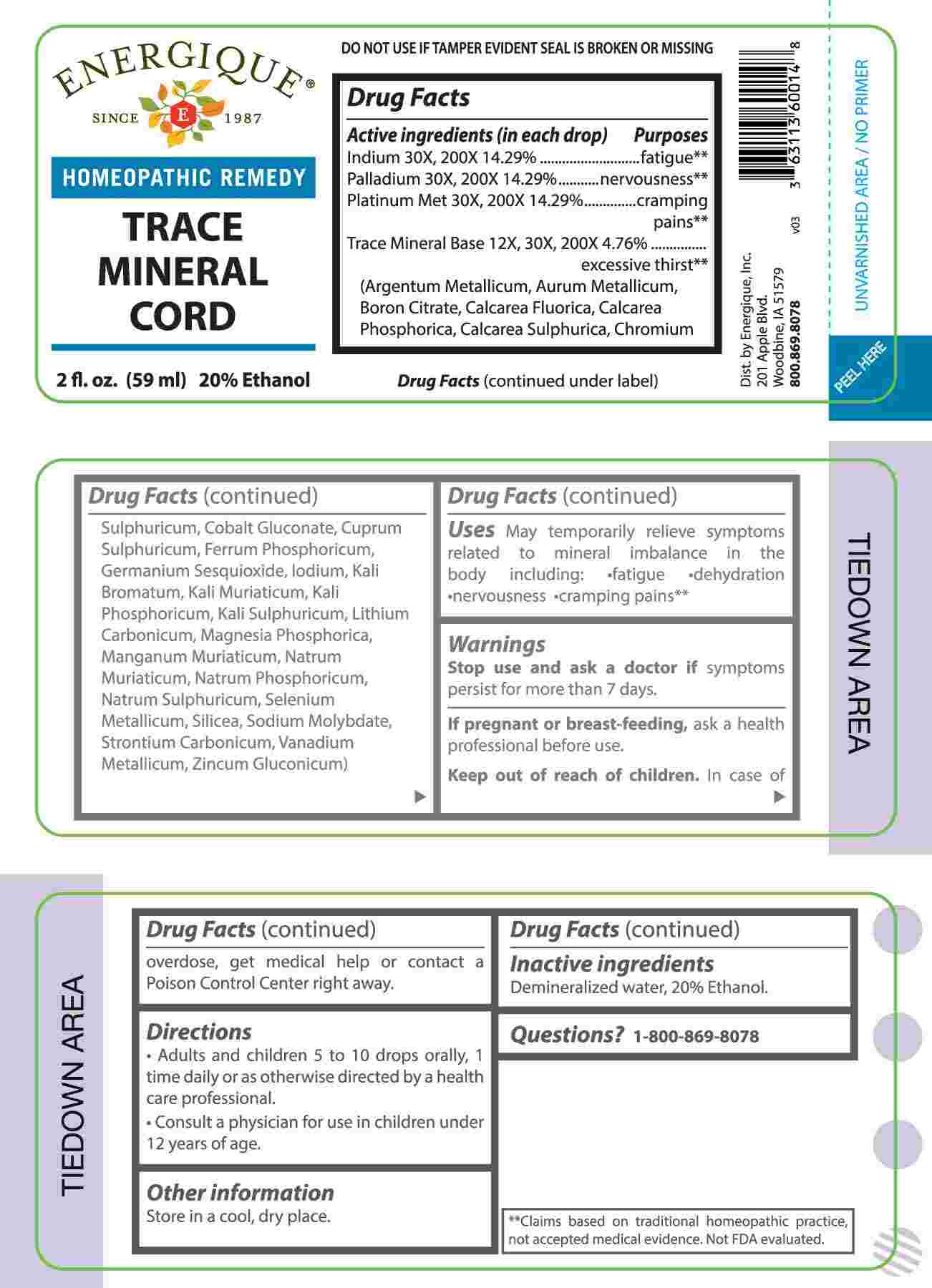 DRUG LABEL: Trace Mineral Cord
NDC: 44911-0724 | Form: LIQUID
Manufacturer: Energique, Inc.
Category: homeopathic | Type: HUMAN OTC DRUG LABEL
Date: 20241219

ACTIVE INGREDIENTS: SILVER 8 [hp_X]/1 mL; GOLD 8 [hp_X]/1 mL; BORON CITRATE 8 [hp_X]/1 mL; CALCIUM FLUORIDE 8 [hp_X]/1 mL; TRIBASIC CALCIUM PHOSPHATE 8 [hp_X]/1 mL; CALCIUM SULFATE ANHYDROUS 8 [hp_X]/1 mL; CHROMIC SULFATE PENTADECAHYDRATE 8 [hp_X]/1 mL; COBALTOUS GLUCONATE 8 [hp_X]/1 mL; CUPRIC SULFATE 8 [hp_X]/1 mL; FERROSOFERRIC PHOSPHATE 8 [hp_X]/1 mL; GERMANIUM SESQUIOXIDE 8 [hp_X]/1 mL; IODINE 8 [hp_X]/1 mL; POTASSIUM BROMIDE 8 [hp_X]/1 mL; POTASSIUM CHLORIDE 8 [hp_X]/1 mL; DIBASIC POTASSIUM PHOSPHATE 8 [hp_X]/1 mL; POTASSIUM SULFATE 8 [hp_X]/1 mL; LITHIUM CARBONATE 8 [hp_X]/1 mL; MAGNESIUM PHOSPHATE, DIBASIC TRIHYDRATE 8 [hp_X]/1 mL; MANGANESE CHLORIDE 8 [hp_X]/1 mL; SODIUM CHLORIDE 8 [hp_X]/1 mL; SODIUM PHOSPHATE, DIBASIC, HEPTAHYDRATE 8 [hp_X]/1 mL; SODIUM SULFATE 8 [hp_X]/1 mL; SELENIUM 8 [hp_X]/1 mL; SILICON DIOXIDE 8 [hp_X]/1 mL; SODIUM MOLYBDATE 8 [hp_X]/1 mL; STRONTIUM CARBONATE 8 [hp_X]/1 mL; VANADIUM 8 [hp_X]/1 mL; ZINC GLUCONATE 8 [hp_X]/1 mL; INDIUM 30 [hp_X]/1 mL; PALLADIUM 30 [hp_X]/1 mL; PLATINUM 30 [hp_X]/1 mL
INACTIVE INGREDIENTS: WATER; ALCOHOL

DRUG FACTS:

ACTIVE INGREDIENTS:

(in each drop) Indium 30X, 200X, 14.29%, Palladium 30X, 200X, 14.29%, Platinum Met 30X, 200X 14.29%, Trace Mineral Base 12X, 30X, 200X 4376% (Argentum Metallicum, Aurum Metallicum, Boron Citrate, Calcarea Fluorica, Calcarea Phosphorica, Calcarea Sulphurica, Chromium Sulphuricum, Cobalt Gluconate, Cuprum Sulphuricum, Ferrum Phosphoricum, Germanium Sesquioxide, Iodium, Kali Bromatum, Kali Muriaticum, Kali Phosphoricum, Kali Sulphuricum, Lithium Carbonicum, Magnesia Phosphorica, Manganum Muriaticum, Natrum Muriaticum, Natrum Phosphoricum, Natrum Sulphuricum, Selenium Metallicum, Silicea, Sodium Molybdate, Strontium Carbonicum, Vanadium Metallicum, Zincum Gluconicum).

PURPOSE:

Indium - fatigue,** Palladium - nervousness,** Platinum Met – cramping pains,** Trace Mineral Base - excessive thirst ** (Argentum Metallicum, Aurum Metallicum, Boron Citrate, Calcarea Fluorica, Calcarea Phosphorica, Calcarea Sulphurica, Chromium Sulphuricum, Cobalt Gluconate, Cuprum Sulphuricum, Ferrum Phosphoricum, Germanium Sesquioxide, Iodium, Kali Bromatum, Kali Muriaticum, Kali Phosphoricum, Kali Sulphuricum, Lithium Carbonicum, Magnesia Phosphorica, Manganum Muriaticum, Natrum Muriaticum, Natrum Phosphoricum, Natrum Sulphuricum, Selenium Metallicum, Silicea, Sodium Molybdate, Strontium Carbonicum, Vanadium Metallicum, Zincum Gluconicum)

**Claims based on traditional homeopathic practice, not accepted medical evidence. Not FDA evaluated.

USES:

May temporarily relieve symptoms related to mineral imbalance in the body including:

•fatigue •dehydration •nervousness •cramping pains**

**Claims based on traditional homeopathic practice, not accepted medical evidence. Not FDA evaluated.

WARNINGS:

Stop use and ask a doctor if symptoms persist for more than 7 days.

If pregnant or breast-feeding, ask a health professional before use.

Keep out of reach of children. In case of overdose, get medical help or contact a Poison Control Center right away.

DO NOT USE IF TAMPER EVIDENT SEAL IS BROKEN OR MISSING

Store in a cool, dry place.

KEEP OUT OF REACH OF CHILDREN:

In case of overdose, get medical help or contact a Poison Control Center right away.

DIRECTIONS:

• Adults and children 5 to 10 drops orally, 1 time daily or as otherwise directed by a health care professional.

Consult a physician for use in children under 12 years of age.

INACTIVE INGREDIENTS:

Demineralized water, 20% Ethanol.

QUESTIONS:

Dist. by Energique, Inc.

201 Apple Blvd.
Woodbine, IA 51579

800.869.8078

PACKAGE LABEL DISPLAY:

ENERGIQUE

SINCE 1987

HOMEOPATHIC REMEDY

TRACE MINERAL

CORD

2 fl. oz. (59 ml)